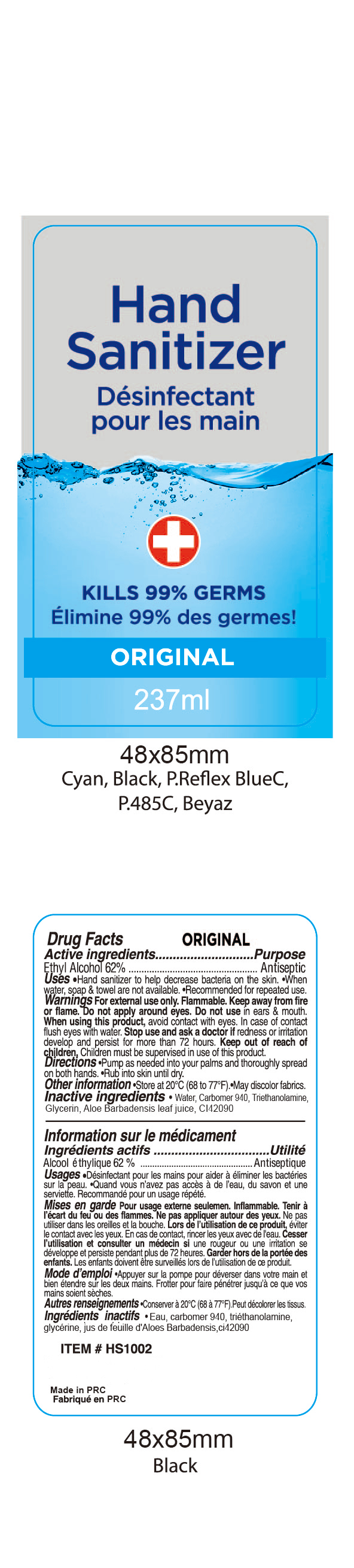 DRUG LABEL: HAND SANITIZER
NDC: 47993-234 | Form: GEL
Manufacturer: NINGBO JIANGBEI OCEAN STAR TRADING CO.,LTD
Category: otc | Type: HUMAN OTC DRUG LABEL
Date: 20201104

ACTIVE INGREDIENTS: ALCOHOL 62 g/112 mL
INACTIVE INGREDIENTS: WATER; TRIETHANOLAMINE BENZOATE 3 g/112 mL; ALOE VERA LEAF 1 g/112 mL; FD&C BLUE NO. 1; GLYCERIN 2 g/112 mL; CARBOMER 940 12 g/112 mL

47993-234

Active ingredients

Ethyl Alcohol 62%

PURPOSE

Antiseptic

Warnings:

For external use only. Flammable. Keep away from fire or flame

DO NOT USE

Do not apply around eyes. Do not use in ears & mouth

When using this product，avoid contact with eyes. In case of contact flush eyes with water.

Stop use and as a doctor if redness or irritation develop and persist for more than 72 hours.

Keep out of reach of children，Children must be supervised in use of this product.

Uses：

Hand sanitizer to help decrease bacteria on the skin.
When water, soap & towel are not available.
Recommended for repeated use.

Directions:

Pump as needed into your palms and thoroughly spread on both hands.
Rub into skin until dry.

OTHER SAFETY INFORMATION

Store at 20 ℃（68 to77℉）
May discolor fabrics.

Inactive Ingredients:

Water,Carbomer 940,Triethanolamine,Glycerin,Aloe barbadensis leaf juice,Fragrance,CI42090